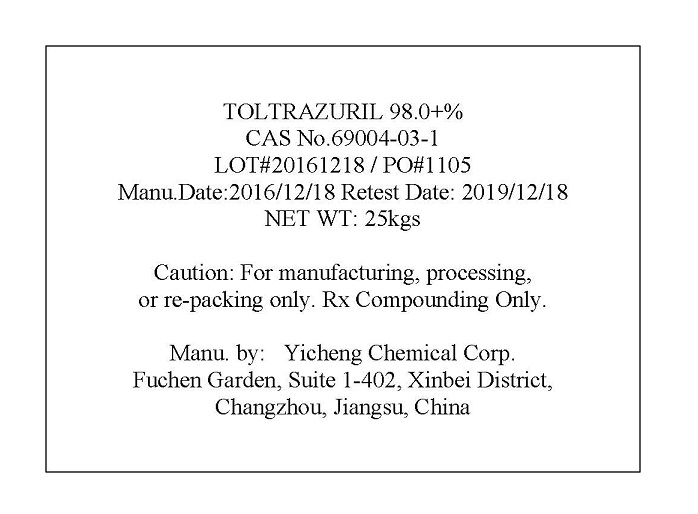 DRUG LABEL: TOLTRAZURIL
NDC: 67995-0519 | Form: POWDER
Manufacturer: Yicheng Chemical Corp.
Category: other | Type: BULK INGREDIENT
Date: 20170711

ACTIVE INGREDIENTS: TOLTRAZURIL 1 kg/1 kg

TOLTRAZURIL-Label